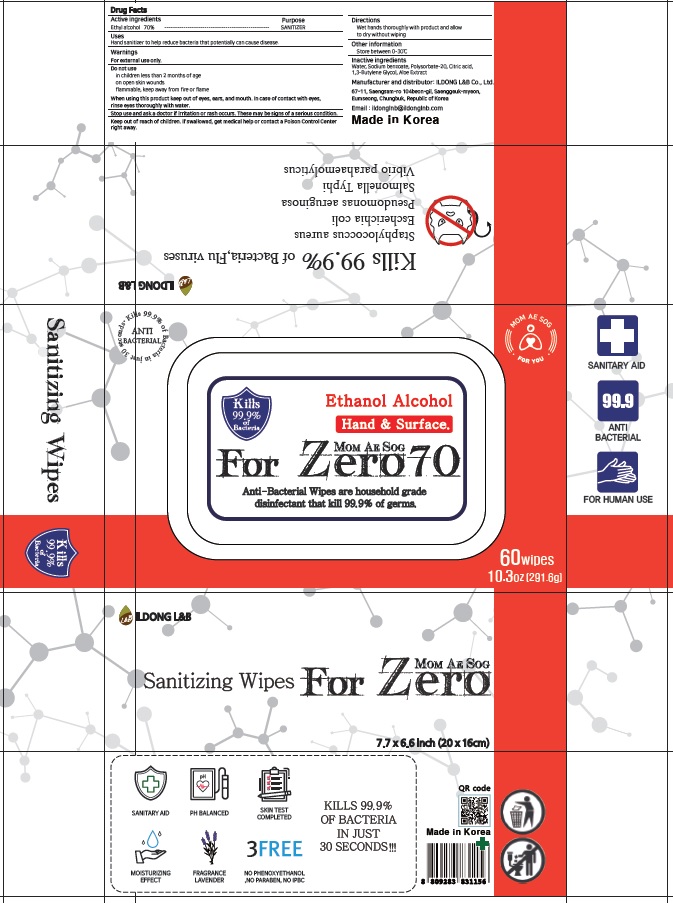 DRUG LABEL: MOM AE SOG FOR ZERO 70
NDC: 78392-020 | Form: LIQUID
Manufacturer: ILDONG L&B CO.,LTD.
Category: otc | Type: HUMAN OTC DRUG LABEL
Date: 20200608

ACTIVE INGREDIENTS: ALCOHOL 70 g/100 g
INACTIVE INGREDIENTS: Water; Sodium benzoate; POLYSORBATE 20; CITRIC ACID MONOHYDRATE; BUTYLENE GLYCOL; ALOE

ACTIVE INGREDIENT

Ethyl alcohol 70%

INACTIVE INGREDIENTS

Water, Sodium benzoate, Polysorbate-20, Citric acid, 1,3-Butylene Glycol, Aloe Extract

PURPOSE

SANITIZER

WARNINGS

For external use only.
--------------------------------------------------------------------------------------------------------
Do not use
• in children less than 2 months of age
• on open skin wounds
• flammable, keep away from fire or flame
--------------------------------------------------------------------------------------------------------
When using this product keep out of eyes, ears, and mouth. In case of contact with eyes, rinse eyes thoroughly with water.
--------------------------------------------------------------------------------------------------------
Stop use and ask a doctor if irritation or rash occurs. These may be signs of a serious condition.

KEEP OUT OF REACH OF CHILDREN

If swallowed, get medical help or contact a Poison Control Center right away.

Uses

Hand sanitizer to help reduce bacteria that potentially can cause disease.

Directions

• Wet hands thoroughly with product and allow to dry without wiping

Other information

• Store between 0-30C